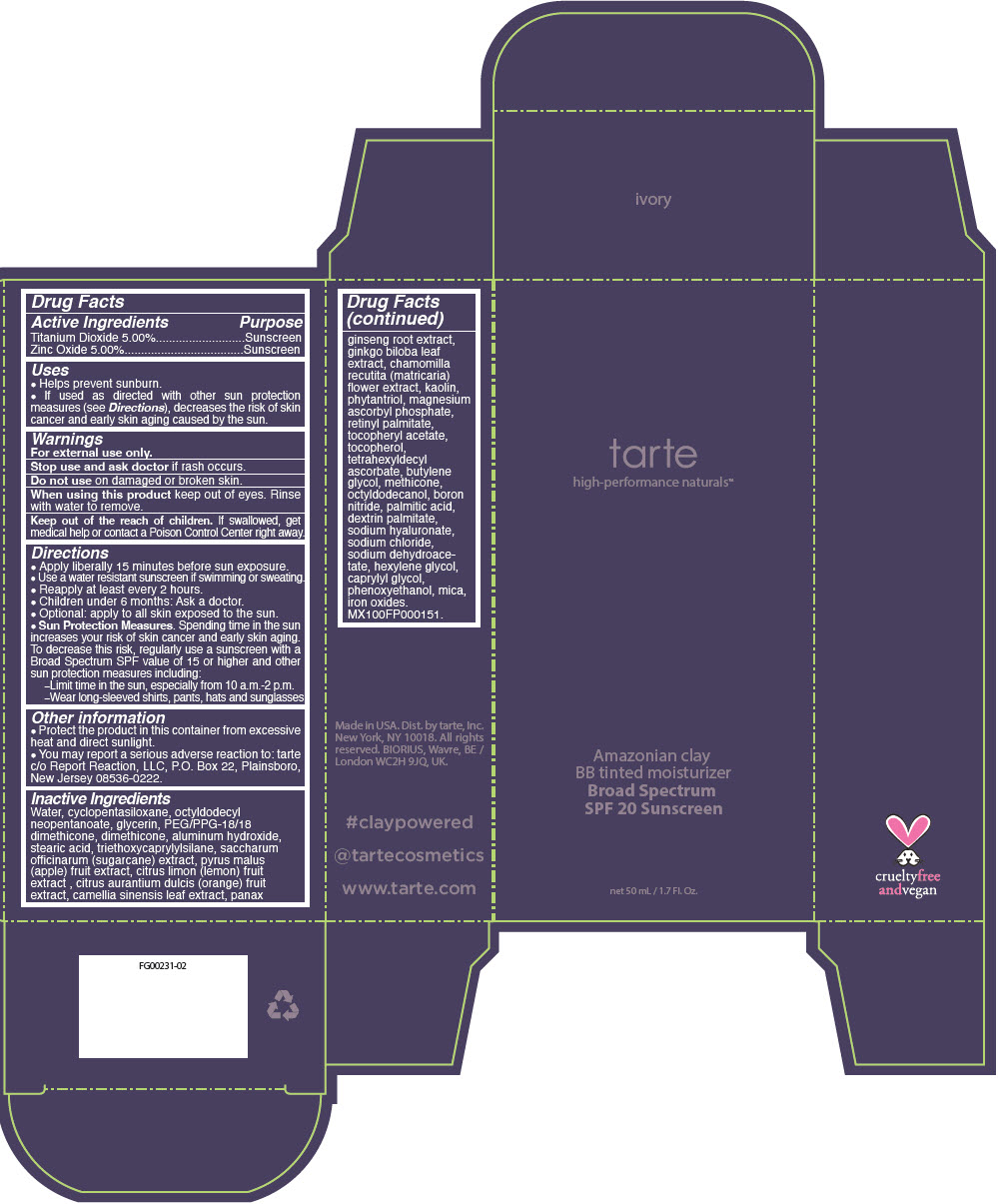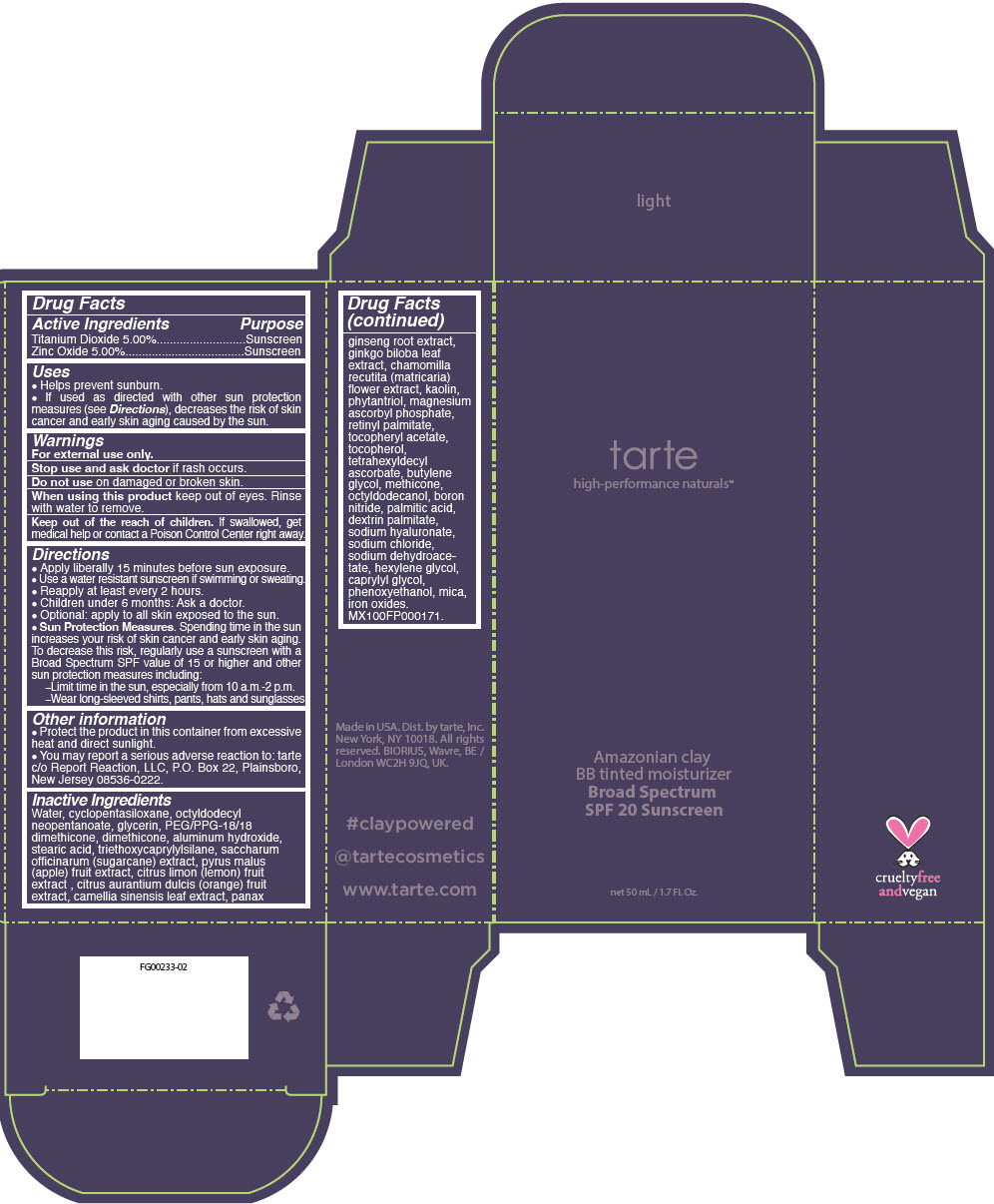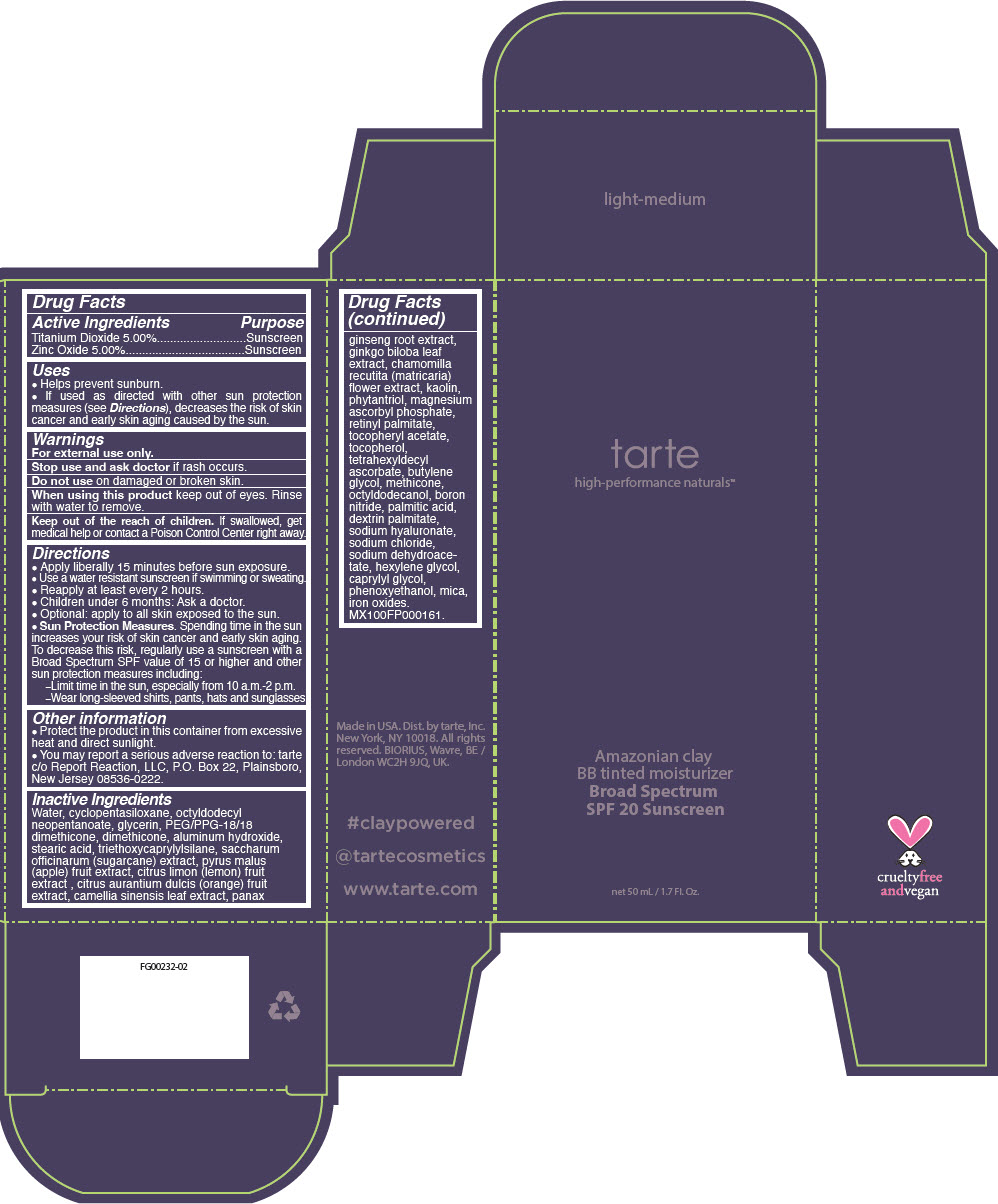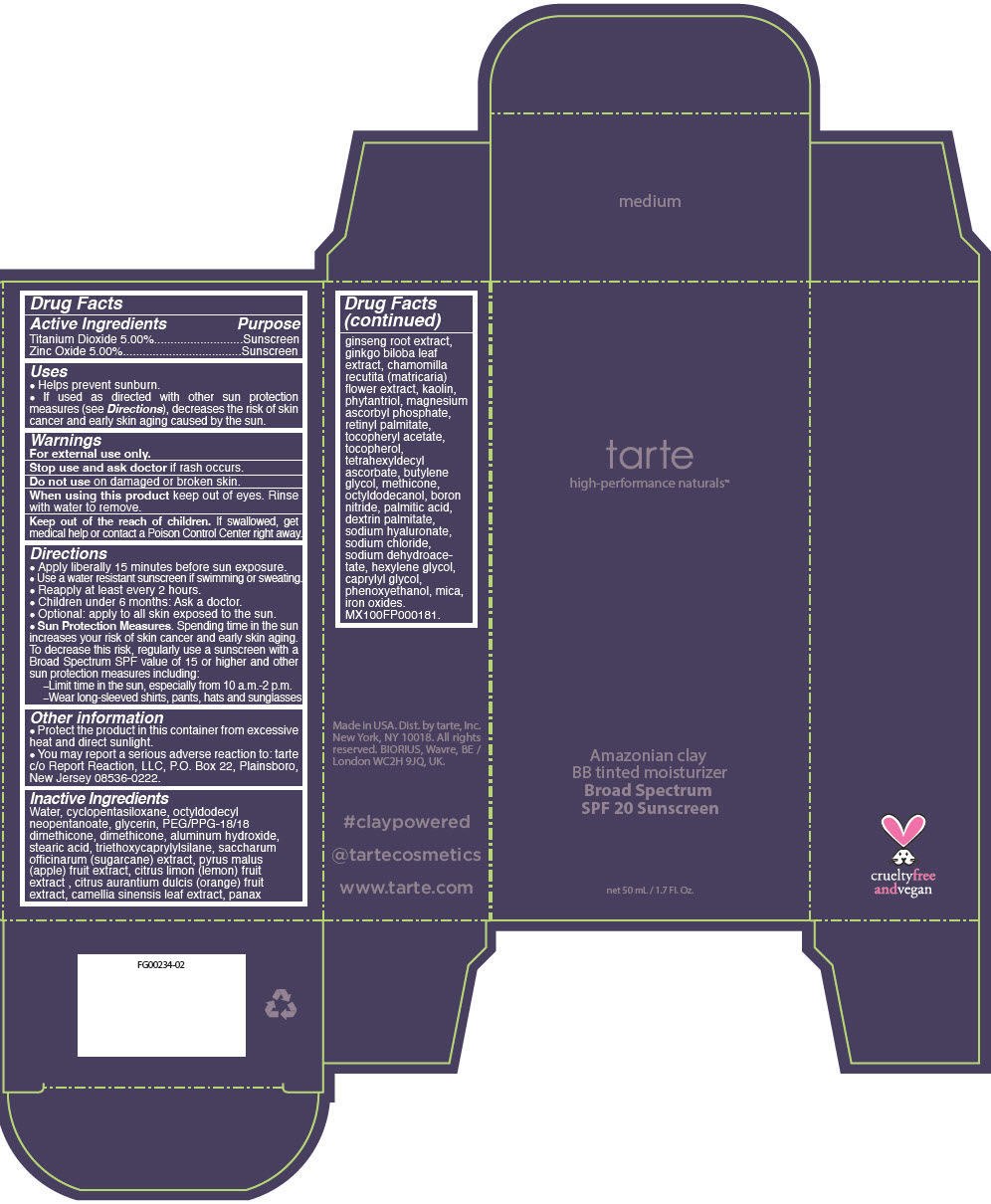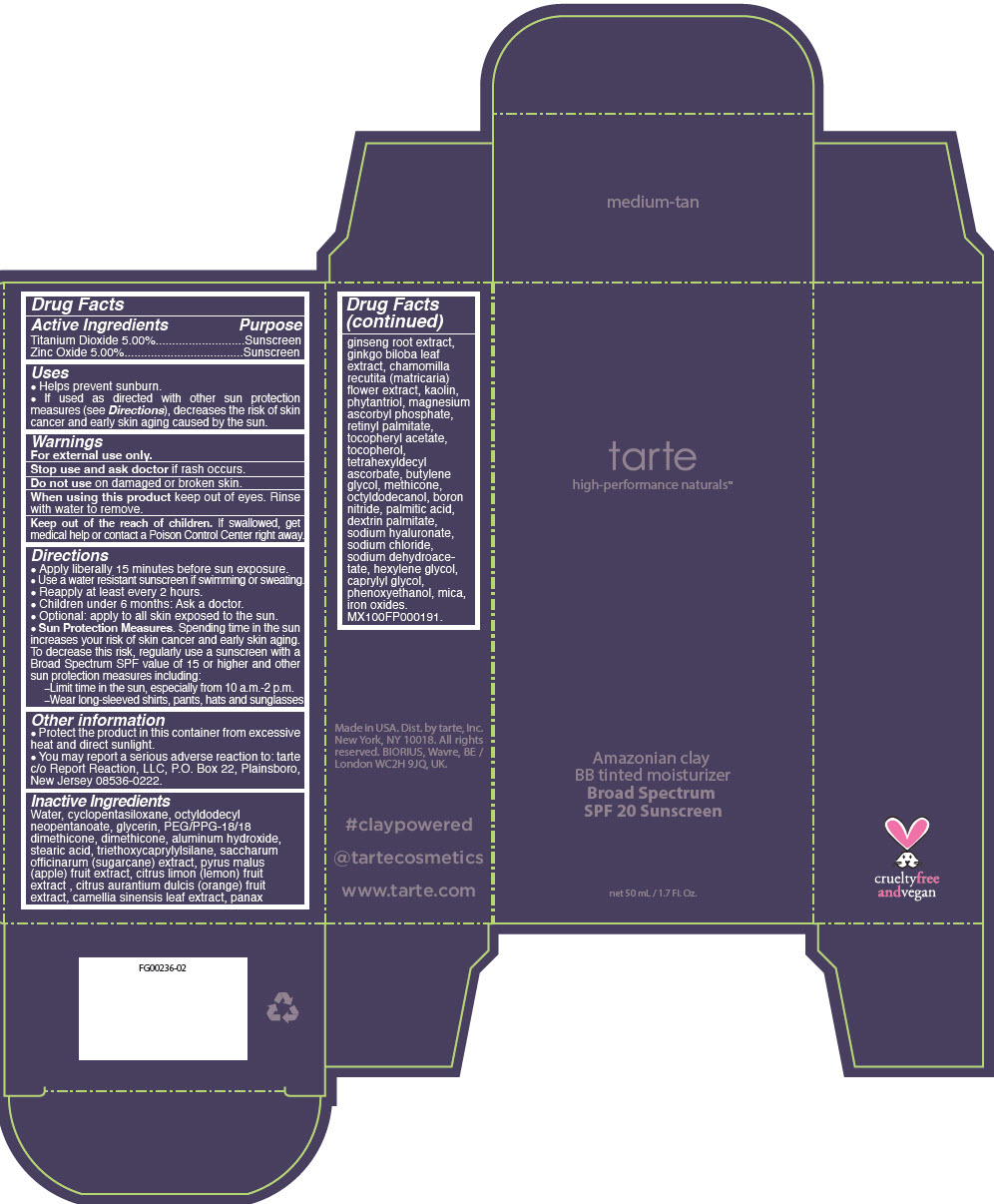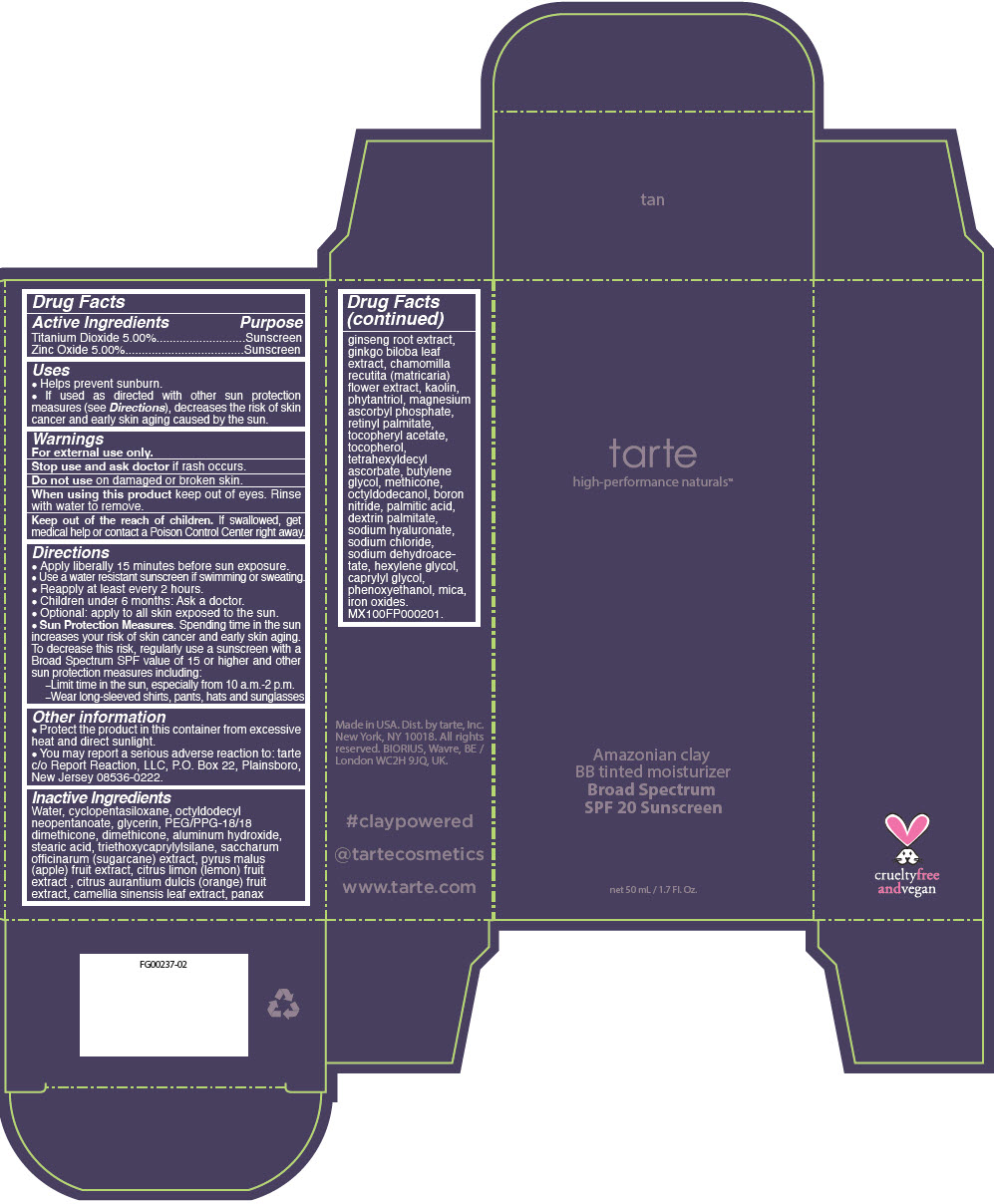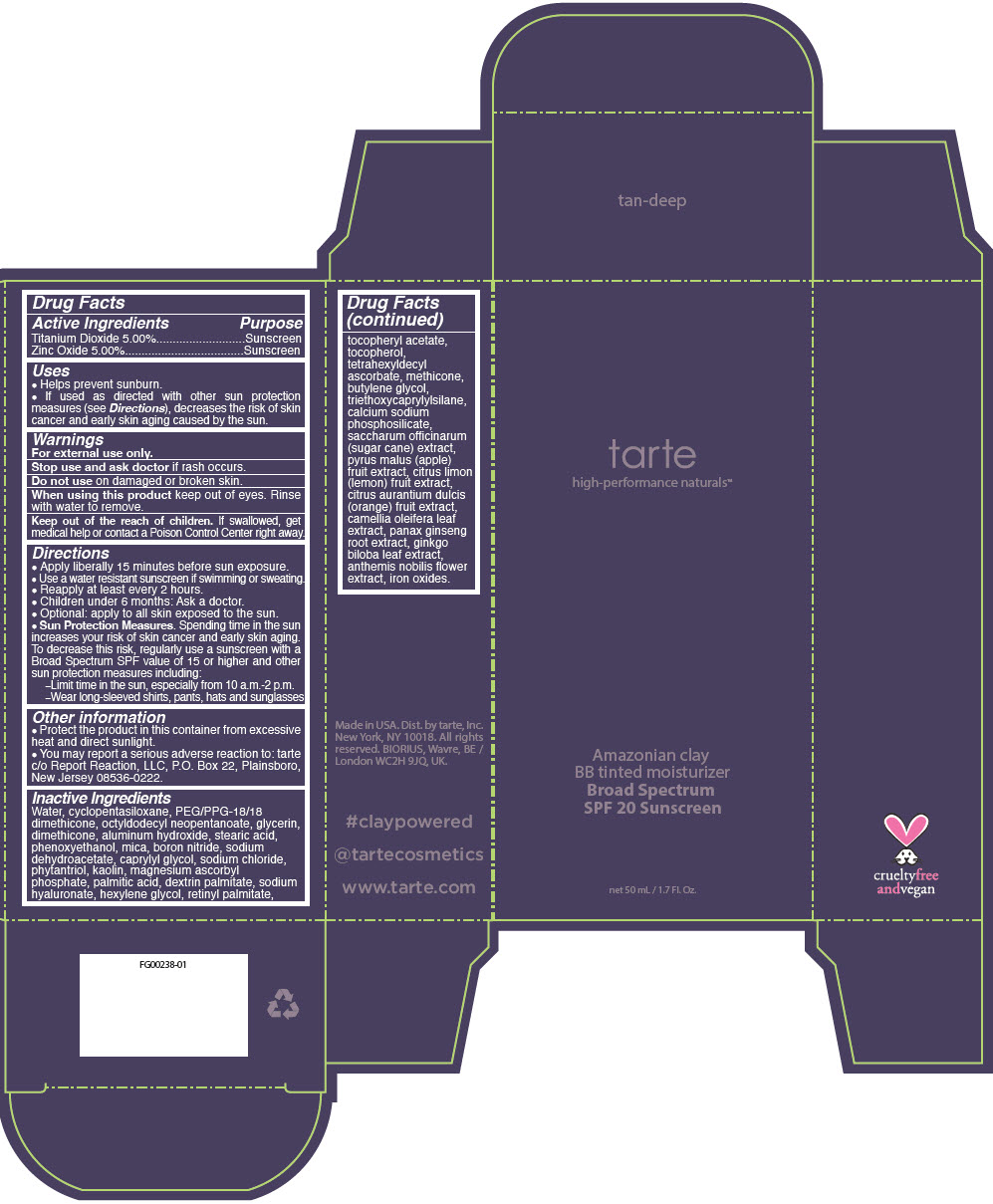 DRUG LABEL: Amazonian Clay BB Tinted Moisturizer Broad Spectrum SPF 20 Sunscreen
NDC: 59735-900 | Form: CREAM
Manufacturer: Mana Products, INC
Category: otc | Type: HUMAN OTC DRUG LABEL
Date: 20240802

ACTIVE INGREDIENTS: TITANIUM DIOXIDE 50 mg/1 mL; ZINC OXIDE 50 mg/1 mL
INACTIVE INGREDIENTS: WATER; CYCLOMETHICONE 5; PEG/PPG-18/18 DIMETHICONE; OCTYLDODECYL NEOPENTANOATE; GLYCERIN; DIMETHICONE; ALUMINUM HYDROXIDE; STEARIC ACID; PHENOXYETHANOL; MICA; BORON NITRIDE; SODIUM DEHYDROACETATE; CAPRYLYL GLYCOL; SODIUM CHLORIDE; PHYTANTRIOL; KAOLIN; MAGNESIUM ASCORBYL PHOSPHATE; PALMITIC ACID; HYALURONATE SODIUM; HEXYLENE GLYCOL; VITAMIN A PALMITATE; .ALPHA.-TOCOPHEROL ACETATE; TOCOPHEROL; TETRAHEXYLDECYL ASCORBATE; BUTYLENE GLYCOL; TRIETHOXYCAPRYLYLSILANE; SUGARCANE; APPLE; LEMON; ORANGE; CAMELLIA OLEIFERA LEAF; ASIAN GINSENG; GINKGO; CHAMAEMELUM NOBILE FLOWER

Amazonian Clay BB Tinted Moisturizer Broad Spectrum SPF 20 Sunscreen

ACTIVE INGREDIENT

Active ingredients | Purpose
Titanium Dioxide 5% | Sunscreen
Zinc Oxide 5% | Sunscreen

Uses

- helps prevent sunburn.
- If used as directed with other sun protection measures (see Directions), decreases the risk of skin cancer and early skin aging caused by the sun

Warnings

For external use only

Stop use and ask doctor if rash occurs

Do not use on damaged or broken skin

When using this product keep out of eyes. Rinse with water to remove.

KEEP OUT OF REACH OF CHILDREN

Keep out of the reach of children. If swallowed, get medical help or contact a Poison Control Center right away.

Directions

- Apply liberally 15 minutes before sun exposure
- Use a water resistant sunscreen if swimming or sweating
- Reapply at least every 2 hours
- Children under 6 months: Ask a doctor
- Optional: apply to all skin exposed to the sun
- Sun Protection Measures. Spending time in the sun increases your risk of skin cancer and early skin aging. To decrease this risk, regularly use a sunscreen with a Broad Spectrum SPF value of 15 or higher and other sun protection measures including:
  - Limit time in the sun, especially from 10 a.m.-2 p.m.
  - Wear long-sleeved shirts, pants, hats and sunglasses

Other information

- Protect the product in this container from excessive heat and direct sunlight
- You may report a serious adverse reaction to: tarte c/o Report Reaction, LLC, P.O. Box 22, Plainsboro, New Jersey 08536-0222.

Inactive ingredients

Water, cyclopentasiloxane, PEG/PPG-18/18 dimethicone, octyldodecyl neopentanoate, glycerin, dimethicone, aluminum hydroxide, stearic acid, phenoxyethanol, mica, boron nitride, sodium dehydroacetate, caprylyl glycol, sodium chloride, phytantriol, kaolin, magnesium ascorbyl phosphate, palmitic acid, dextrin palmitate, sodium hyaluronate, hexylene glycol, retinyl palmitate, tocopheryl acetate, tocopherol, tetrahexyldecyl ascorbate, methicone, butylene glycol, triethoxycaprylylsilane, calcium sodium phosphosilicate, saccharum officinarum (sugar cane) extract, pyrus malus (apple) fruit extract, citrus limon (lemon) fruit extract, citrus aurantium dulcis (orange) fruit extract, camellia oleifera leaf extract, panax ginseng root extract, ginkgo biloba leaf extract, anthemis nobilis flower extract, iron oxides.

Dist. by tarte™, Inc. New York, NY 10018.

PRINCIPAL DISPLAY PANEL - 50 mL Tube Carton - ivory

tarte
high-performance naturals™

Amazonian clay
BB tinted moisturizer
Broad Spectrum
SPF 20 Sunscreen

net 50 mL / 1.7 Fl. Oz.

PRINCIPAL DISPLAY PANEL - 50 mL Tube Carton - light

tarte
high-performance naturals™

Amazonian clay
BB tinted moisturizer
Broad Spectrum
SPF 20 Sunscreen

net 50 mL / 1.7 Fl. Oz.

PRINCIPAL DISPLAY PANEL - 50 mL Tube Carton - light-medium

tarte
high-performance naturals™

Amazonian clay
BB tinted moisturizer
Broad Spectrum
SPF 20 Sunscreen

net 50 mL / 1.7 Fl. Oz.

PRINCIPAL DISPLAY PANEL - 50 mL Tube Carton - medium

tarte
high-performance naturals™

Amazonian clay
BB tinted moisturizer
Broad Spectrum
SPF 20 Sunscreen

net 50 mL / 1.7 Fl. Oz.

PRINCIPAL DISPLAY PANEL - 50 mL Tube Carton - medium-tan

tarte
high-performance naturals™

Amazonian clay
BB tinted moisturizer
Broad Spectrum
SPF 20 Sunscreen

net 50 mL / 1.7 Fl. Oz.

PRINCIPAL DISPLAY PANEL - 50 mL Tube Carton - tan

tarte
high-performance naturals™

Amazonian clay
BB tinted moisturizer
Broad Spectrum
SPF 20 Sunscreen

net 50 mL / 1.7 Fl. Oz.

PRINCIPAL DISPLAY PANEL - 50 mL Tube Carton - tan-deep

tarte
high-performance naturals™

Amazonian clay
BB tinted moisturizer
Broad Spectrum
SPF 20 Sunscreen

net 50 mL / 1.7 Fl. Oz.